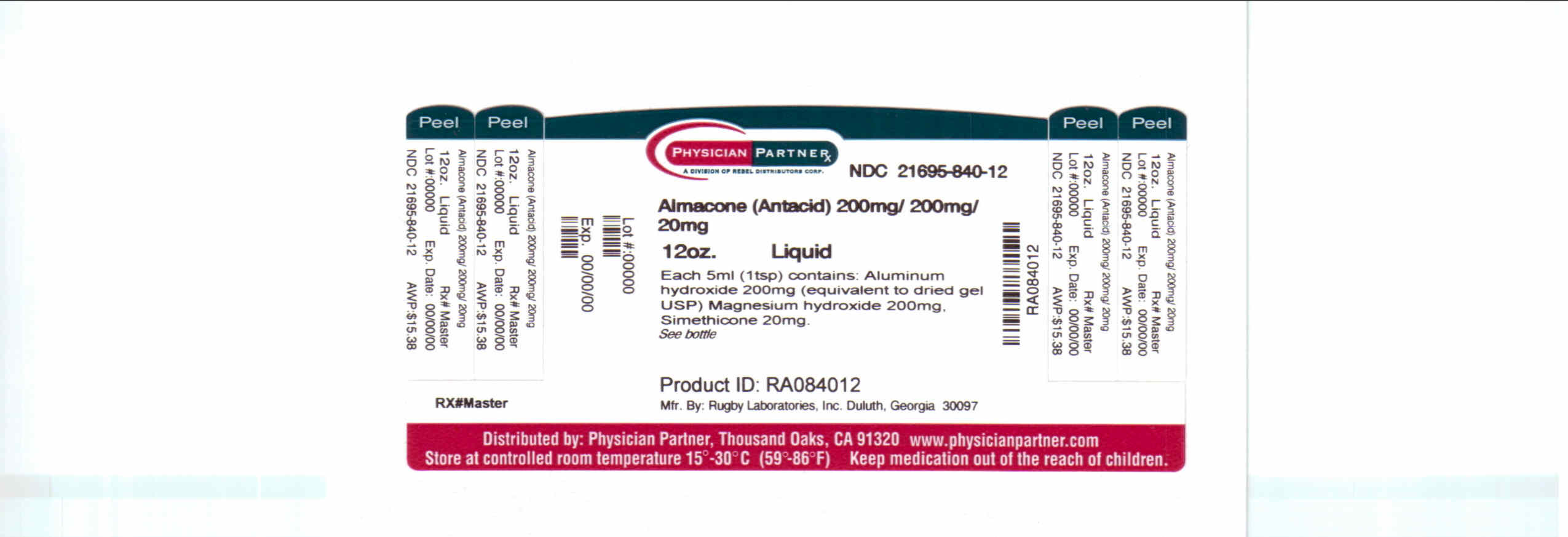 DRUG LABEL: Almacone
NDC: 21695-840 | Form: LIQUID
Manufacturer: Rebel Distributors Corp
Category: otc | Type: HUMAN OTC DRUG LABEL
Date: 20110215

ACTIVE INGREDIENTS: ALUMINUM HYDROXIDE 200 mg/5 mL; MAGNESIUM HYDROXIDE 200 mg/5 mL
INACTIVE INGREDIENTS: BENZYL ALCOHOL; BUTYLPARABEN; CELLULOSE, MICROCRYSTALLINE; CARBOXYMETHYLCELLULOSE; HYPROMELLOSES; PROPYLPARABEN; WATER; SACCHARIN SODIUM; SORBITOL

Almacone Drug Facts

Active ingredients

Aluminum Hydroxide 200mg

Magnesium Hydroxide 200mg

Uses

Use(s)

Enter section text here

Uses relieves

• heartburn

• acid indigestion

• sour stomach

• gas associated with these conditions

Warnings

Ask a doctor before use if you have

• kidney disease

• a magnesium restricted diet

Ask a doctor or pharmacist before use if you are taking a prescription drug. Antacids may interact with certain prescription drugs.

Stop use and ask a doctor if syptoms last more than 2 weeks.

KEEP OUT OF REACH OF CHILDREN.

TAMPER EVIDENT: DO NOT USE IF IMPRINTED SAFETY SEAL UNDER CAP IS BROKEN OR MISSING

Directions

Shake well before use. Do not take more than 24 teaspoonful in 24 hours or use the maximum dosage for more than 2 weeks. Adults and children 12 years and older: take 2 to 4 teaspoonsfuls between meals, at bedtime, or as directed by a doctor.

Children under 12 years: ask a doctor.

Other Information

Each 5 mL teaspoon contains:

magnesium 25 mg, sodium 1 mg. Store at room temperature. Protect from freezing. Keep tighly closed.

Inactive ingredients

Benzoyl alcohol, butylparaben, carboxy methylcellulose sodium, flavor, hypromelloses, microcrystalline cellulose, propylparaben, purified water, saccharin sodium, sorbitol solution.

How Supplied

Almacone (antacid) is supplied in 12 oz. bottles NDC 21695-840-12

Questions or comments?

Call 1-800-645-2158, 9 am - 5 pm EST, Monday-Friday.

Distributed by:

Rugby Laboratories

Duluth, GA 30097

Repackaged by:

Rebel Distributors Corp

Thousand Oaks, CA 91320